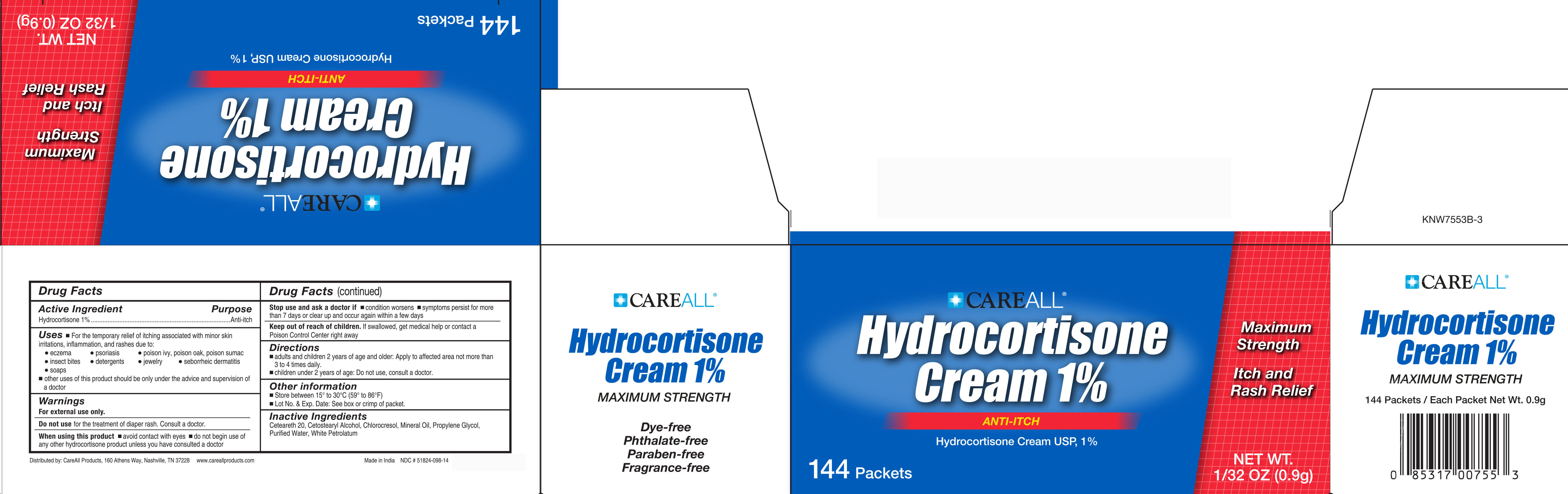 DRUG LABEL: CAREALL Hydrocortisone 

NDC: 51824-098 | Form: CREAM
Manufacturer: New World Imports, Inc
Category: otc | Type: HUMAN OTC DRUG LABEL
Date: 20251201

ACTIVE INGREDIENTS: HYDROCORTISONE 0.01 g/1 g
INACTIVE INGREDIENTS: PROPYLENE GLYCOL; WHITE PETROLATUM; MINERAL OIL; CETOSTEARYL ALCOHOL; POLYOXYL 20 CETOSTEARYL ETHER; CHLOROCRESOL; WATER

Drug Facts

Active Ingredient

Hydrocortisone 1%

Purpose

Anti-Itch

Keep out of reach of children. If swallowed, get medical help or contact a Poison Control Center right away

Uses

- For the temporary relief of itching associated with minor skin irritations, inflammation, and rashes due to: eczema, psoriasis, poison ivy, oak & sumac, insect bites, detergents, jewelry, seborrheic dermatitis, and soap
- Other uses of this product should be only under the advice and supervision of a doctor

Warnings

For external use only

Do not use: For the treatment of diaper rash. Consult a doctor

When using this product:

Avoid contact with the eyes

Do not begin use of any other hydrocortisone product unless you have consulted a doctor

Stop use and ask a doctor if:

Condition worsens

Symptoms persist for more than 7 days or clear up and occur again within a few days

Directions

- Adults and children 2 years of age and older: apply to affected area not more than 3 to 4 times daily.
- Children under 2 years of age do not use. Ask a doctor.

INACTIVE INGREDIENT

Ceteareth 20, Cetostearyl Alcohol, Chlorocresol, Mineral Oil, Propylene Glycol, Purified Water, White Petrolatum